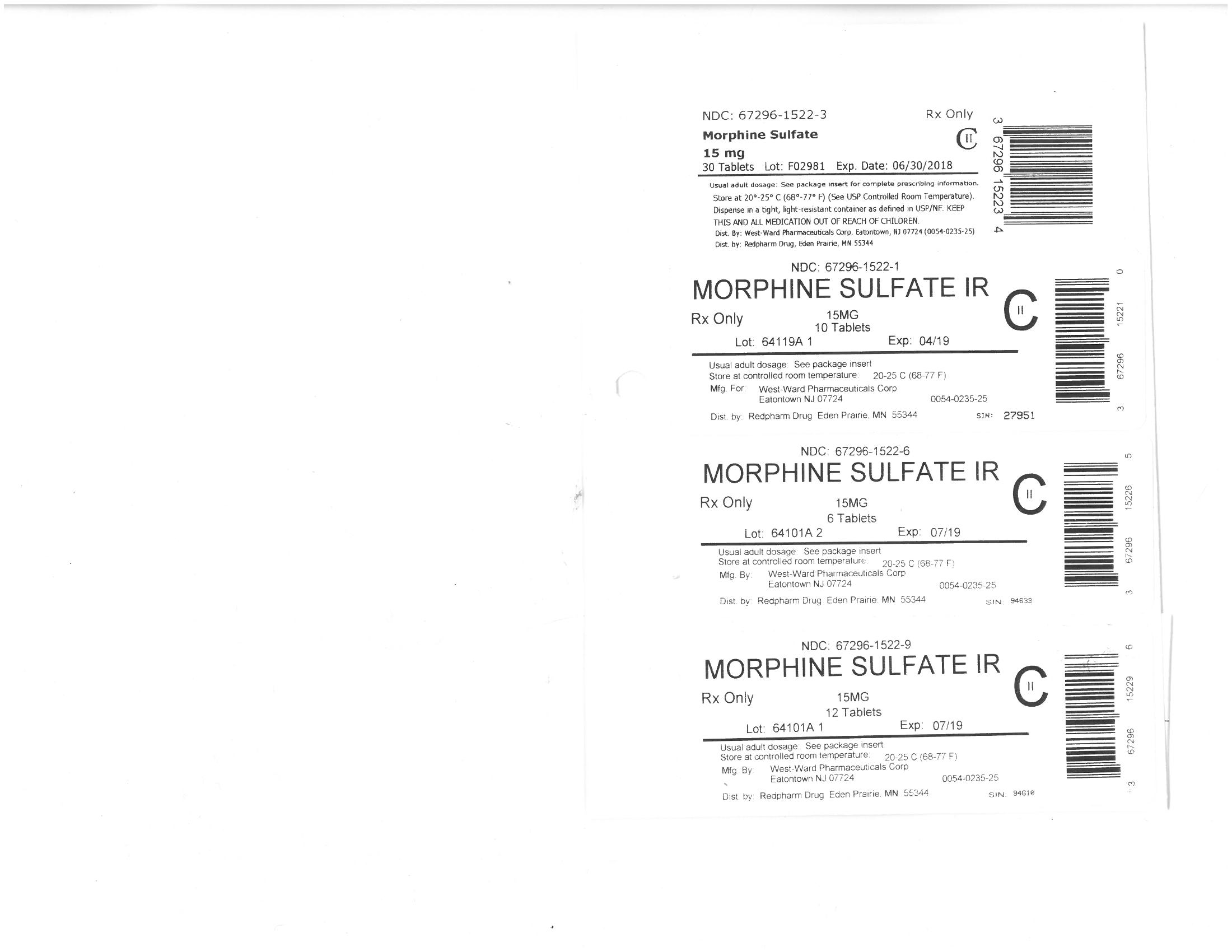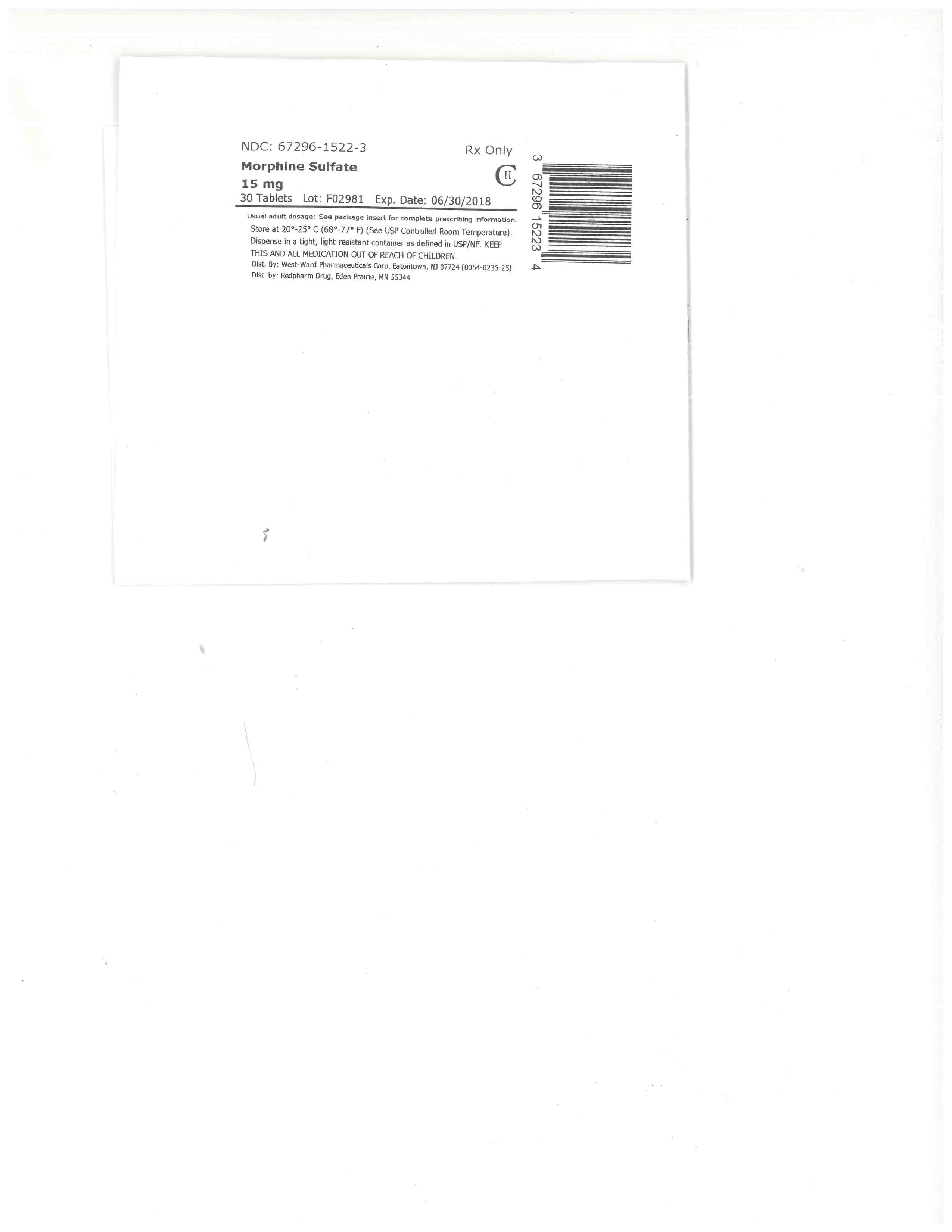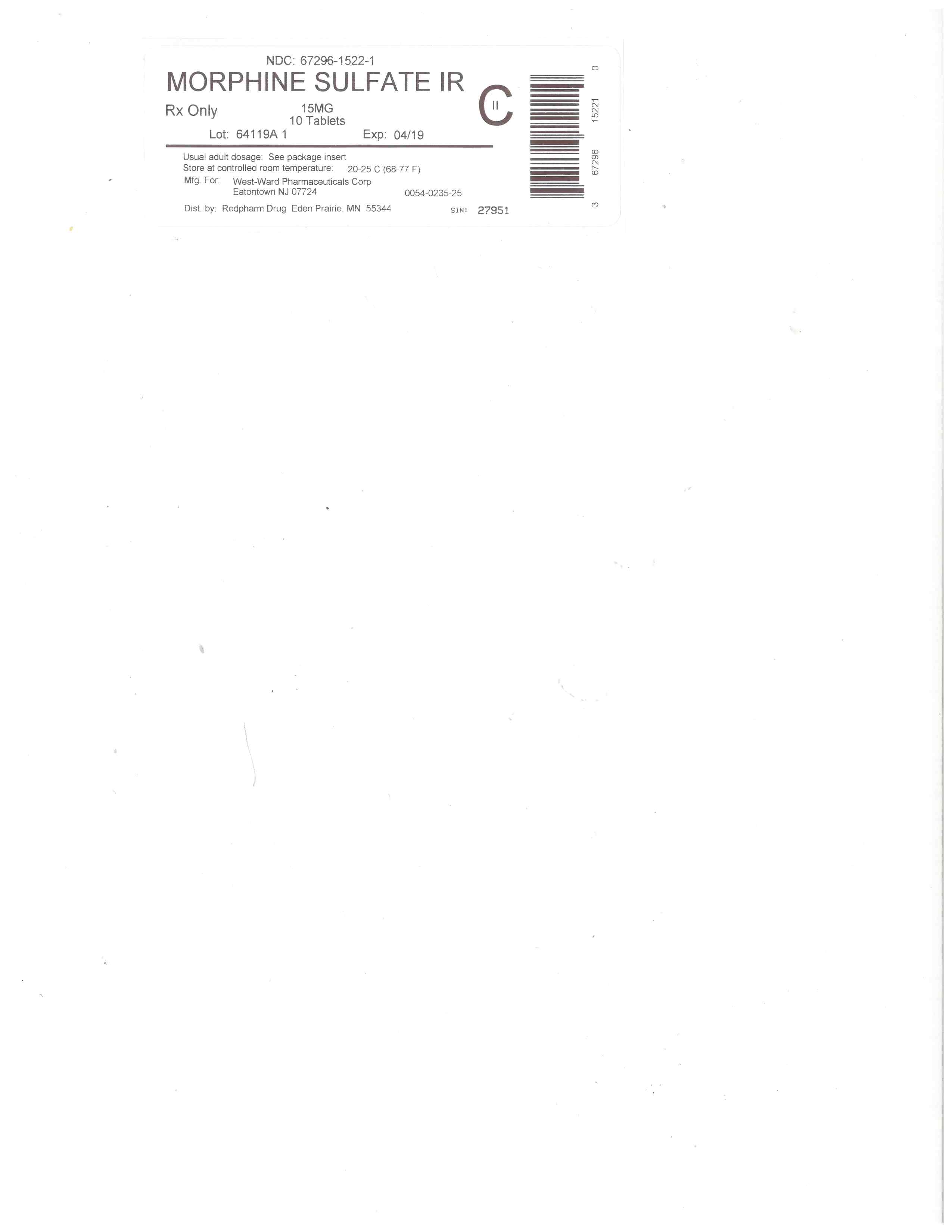 DRUG LABEL: Morphine Sulfate
NDC: 67296-1522 | Form: TABLET
Manufacturer: RedPharm Drug, Inc.
Category: prescription | Type: HUMAN PRESCRIPTION DRUG LABEL
Date: 20240801
DEA Schedule: CII

ACTIVE INGREDIENTS: MORPHINE SULFATE 15 mg/1 1
INACTIVE INGREDIENTS: SILICON DIOXIDE; STARCH, CORN; CELLULOSE, MICROCRYSTALLINE; STEARIC ACID

BOXED WARNING

WARNING: ADDICTION, ABUSE, AND MISUSE; LIFE-THREATENING RESPIRATORY DEPRESSION; ACCIDENTAL INGESTION; NEONATAL OPIOID WITHDRAWAL SYNDROME; AND RISKS FROM CONCOMITANT USE WITH BENZODIAZEPINES OR OTHER CNS DEPRESSANTS

Addiction, Abuse, and Misuse

Morphine Sulfate Tablets expose patients and other users to the risks of opioid addiction, abuse, and misuse, which can lead to overdose and death. Assess each patient’s risk prior to prescribing Morphine Sulfate Tablets, and monitor all patients regularly for the development of these behaviors and conditions [see Warnings and Precautions (5.1)].

Life-Threatening Respiratory Depression

Serious, life-threatening, or fatal respiratory depression may occur with use of Morphine Sulfate Tablets. Monitor for respiratory depression, especially during initiation of Morphine Sulfate Tablets or following a dose increase [see Warnings and Precautions (5.2)].

Accidental Ingestion

Accidental ingestion of even one dose of Morphine Sulfate Tablets, especially by children, can result in a fatal overdose of morphine [see Warnings and Precautions (5.2)].

Neonatal Opioid Withdrawal Syndrome

Prolonged use of Morphine Sulfate Tablets during pregnancy can result in neonatal opioid withdrawal syndrome, which may be life-threatening if not recognized and treated, and requires management according to protocols developed by neonatology experts. If opioid use is required for a prolonged period in a pregnant woman, advise the patient of the risk of neonatal opioid withdrawal syndrome and ensure that appropriate treatment will be available [see Warnings and Precautions (5.3)].

Risks From Concomitant Use With Benzodiazepines Or Other CNS Depressants

Concomitant use of opioids with benzodiazepines or other central nervous system (CNS) depressants, including alcohol, may result in profound sedation, respiratory depression, coma, and death [see Warnings and Precautions (5.4), Drug Interactions (7)].

•
Reserve concomitant prescribing of Morphine Sulfate Tablets and benzodiazepines or other CNS depressants for use in patients for whom alternative treatment options are inadequate.
•
Limit dosages and durations to the minimum required.
•
Follow patients for signs and symptoms of respiratory depression and sedation.

HIGHLIGHTS OF PRESCRIBING INFORMATION

These highlights do not include all the information needed to use Morphine Sulfate Tablets safely and effectively. See full prescribing information for Morphine Sulfate Tablets.
Morphine Sulfate tablets, for oral use CII
Initial U.S. Approval: 1941

WARNING: ADDICTION, ABUSE, AND MISUSE; LIFE-THREATENING RESPIRATORY DEPRESSION; ACCIDENTAL INGESTION; NEONATAL OPIOID WITHDRAWAL SYNDROME; AND RISKS FROM CONCOMITANT USE WITH BENZODIAZEPINES OR OTHER CNS DEPRESSANTS
SEE FULL PRESCRIBING INFORMATION FOR COMPLETE BOXED WARNING.

•
Morphine Sulfate Tablets expose users to risks of addiction, abuse, and misuse, which can lead to overdose and death. Assess patient’s risk before prescribing and monitor regularly for these behaviors and conditions. (5.1)
•
Serious, life-threatening, or fatal respiratory depression may occur. Monitor closely, especially upon initiation or following a dose increase. (5.2)
•
Accidental ingestion of Morphine Sulfate Tablets, especially by children, can result in a fatal overdose of morphine. (5.2)
•
Prolonged use of Morphine Sulfate Tablets during pregnancy can result in neonatal opioid withdrawal syndrome, which may be life-threatening if not recognized and treated. If prolonged opioid use is required in a pregnant woman, advise the patient of the risk of neonatal opioid withdrawal syndrome and ensure that appropriate treatment will be available. (5.3)
•
Concomitant use of opioids with benzodiazepines or other central nervous system (CNS) depressants, including alcohol, may result in profound sedation, respiratory depression, coma, and death. Reserve concomitant prescribing for use in patients for whom alternative treatment options are inadequate; limit dosages and durations to the minimum required; and follow patients for signs and symptoms of respiratory depression and sedation. (5.4, 7)

RECENT MAJOR CHANGES

Boxed Warning

12/2016

Indications and Usage (1)

12/2016

Dosage and Administration (2)

12/2016

Contraindications (4)

12/2016

Warnings and Precautions (5)

12/2016

INDICATIONS AND USAGE

Morphine Sulfate Tablets are an opioid agonist indicated for the management of acute and chronic pain severe enough to require an opioid analgesic and for which alternative treatments are inadequate. (1)

Limitations of Use (1)

Because of the risks of addiction, abuse, and misuse with opioids, even at recommended doses, reserve Morphine Sulfate Tablets for use in patients for whom alternative treatment options [e.g., non-opioid analgesics or opioid combination products]:

•
Have not been tolerated, or are not expected to be tolerated,
•
Have not provided adequate analgesia, or are not expected to provide adequate analgesia.

DOSAGE AND ADMINISTRATION

•
Use the lowest effective dosage for the shortest duration consistent with individual patient treatment goals. (2.1)
•
Individualize dosing based on the severity of pain, patient response, prior analgesic experience, and risk factors for addiction, abuse, and misuse. (2.1)
•
Initiate Treatment with Morphine Sulfate Tablets: 15 to 30 mg every 4 hours as needed. (2.2)
•
Do not stop Morphine Sulfate Tablets abruptly in a physically dependent patient. (2.4)

DOSAGE FORMS AND STRENGTHS

Tablets: 15 mg and 30 mg. (3)

CONTRAINDICATIONS

•
Significant respiratory depression. (4)
•
Acute or severe bronchial asthma in an unmonitored setting or in absence of resuscitative equipment. (4)
•
Concurrent use of monoamine oxidase inhibitors (MAOIs) or use of MAOIs within the last 14 days. (4)
•
Known or suspected gastrointestinal obstruction, including paralytic ileus. (4)
•
Hypersensitivity to morphine. (4)

WARNINGS AND PRECAUTIONS

•
Life-Threatening Respiratory Depression in Patients with Chronic Pulmonary Disease or in Elderly, Cachectic, or Debilitated Patients: Monitor closely, particularly during initiation and titration. (5.5)
•
Adrenal Insufficiency: If diagnosed, treat with physiologic replacement of corticosteroids, and wean patient off of the opioid. (5.7)
•
Severe Hypotension: Monitor during dosage initiation and titration. Avoid use of Morphine Sulfate Tablets in patients with circulatory shock. (5.8)
•
Risks of Use in Patients with Increased Intracranial Pressure, Brain Tumors, Head Injury, or Impaired Consciousness: Monitor for sedation and respiratory depression. Avoid use of Morphine Sulfate Tablets in patients with impaired consciousness or coma. (5.9)

ADVERSE REACTIONS

Most Common Adverse Reactions Seen on Initiation of Therapy are: constipation, nausea, somnolence, lightheadedness, dizziness, sedation, vomiting, and sweating. (6)

To report SUSPECTED ADVERSE REACTIONS, contact West-Ward Pharmaceuticals Corp. at 1-800-962-8364 or FDA at 1-800-FDA-1088 or WWW.FDA.GOV/MEDWATCH.

DRUG INTERACTIONS

•
Serotonergic Drugs: Concomitant use may result in serotonin syndrome. Discontinue Morphine Sulfate Tablets if serotonin syndrome is suspected. (7)
•
Mixed Agonist/Antagonist and Partial Agonist Opioid Analgesics: Avoid use with Morphine Sulfate Tablets because they may reduce analgesic effect of Morphine Sulfate Tablets or precipitate withdrawal symptoms. (7)

USE IN SPECIFIC POPULATIONS

•
Pregnancy: May cause fetal harm. (8.1)

See 17 for PATIENT COUNSELING INFORMATION and Medication Guide.

Revised: 4/2017

FULL PRESCRIBING INFORMATION: CONTENTS*

WARNING: ADDICTION, ABUSE, AND MISUSE; LIFE-THREATENING RESPIRATORY DEPRESSION; ACCIDENTAL INGESTION; NEONATAL OPIOID WITHDRAWAL SYNDROME; AND RISKS FROM CONCOMITANT USE WITH BENZODIAZEPINES OR OTHER CNS DEPRESSANTS
1 INDICATIONS AND USAGE
2 DOSAGE AND ADMINISTRATION
2.1 Important Dosage and Administration Instructions
2.2 Initial Dosage
2.3 Titration and Maintenance of Therapy
2.4 Discontinuation of Morphine Sulfate Tablets
3 DOSAGE FORMS AND STRENGTHS
4 CONTRAINDICATIONS
5 WARNINGS AND PRECAUTIONS
5.1 Addiction, Abuse, and Misuse
5.2 Life-Threatening Respiratory Depression
5.3 Neonatal Opioid Withdrawal Syndrome
5.4 Risks from Concomitant Use with Benzodiazepines or Other CNS Depressants
5.5 Life-Threatening Respiratory Depression in Patients with Chronic Pulmonary Disease or in Elderly, Cachectic, or Debilitated Patients
5.6 Interaction with Monoamine Oxidase Inhibitors
5.7 Adrenal Insufficiency
5.8 Severe Hypotension
5.9 Risks of Use in Patients with Increased Intracranial Pressure, Brain Tumors, Head Injury, or Impaired Consciousness
5.10 Risks of Use in Patients with Gastrointestinal Conditions
5.11 Increased Risk of Seizures in Patients with Seizure Disorders
5.12 Withdrawal
5.13 Risks of Driving and Operating Machinery
6 ADVERSE REACTIONS
7 DRUG INTERACTIONS
8 USE IN SPECIFIC POPULATIONS
8.1 Pregnancy
8.2 Lactation
8.3 Females and Males of Reproductive Potential
8.4 Pediatric Use
8.5 Geriatric Use
8.6 Hepatic Impairment
8.7 Renal Impairment
9 DRUG ABUSE AND DEPENDENCE
9.1 Controlled Substance
9.2 Abuse
9.3 Dependence
10 OVERDOSAGE
11 DESCRIPTION
12 CLINICAL PHARMACOLOGY
12.1 Mechanism of Action
12.2 Pharmacodynamics
12.3 Pharmacokinetics
13 NONCLINICAL TOXICOLOGY
13.1 Carcinogenesis, Mutagenesis, Impairment of Fertility
16 HOW SUPPLIED/STORAGE AND HANDLING
17 PATIENT COUNSELING INFORMATION

*
Sections or subsections omitted from the full prescribing information are not listed.

1 INDICATIONS AND USAGE

Morphine Sulfate Tablets are indicated for the management of acute and chronic pain severe enough to require an opioid analgesic and for which alternative treatments are inadequate.

Limitations of Use

Because of the risks of addiction, abuse, and misuse with opioids, even at recommended doses [see Warnings and Precautions (5.1)], reserve Morphine Sulfate Tablets for use in patients for whom alternative treatment options [e.g., non-opioid analgesics or opioid combination products]:

•
Have not been tolerated, or are not expected to be tolerated,
•
Have not provided adequate analgesia, or are not expected to provide adequate analgesia.

2 DOSAGE AND ADMINISTRATION

2.1 Important Dosage and Administration Instructions

Use the lowest effective dosage for the shortest duration consistent with individual patient treatment goals [see Warnings and Precautions (5)].

Initiate the dosing regimen for each patient individually, taking into account the patient's severity of pain, patient response, prior analgesic treatment experience, and risk factors for addiction, abuse, and misuse [see Warnings and Precautions (5.1)].

Monitor patients closely for respiratory depression, especially within the first 24 to 72 hours of initiating therapy and following dosage increases with morphine sulfate and adjust the dosage accordingly [see Warnings and Precautions (5.2)].

2.2 Initial Dosage

Use of Morphine Sulfate Tablets as the First Opioid Analgesic (Opioid-naïve or Opioid-non-tolerant Patients)

Initiate treatment with Morphine Sulfate Tablets in a dosing range of 15 mg to 30 mg every 4 hours as needed for pain.

Conversion from Parenteral Morphine to Morphine Sulfate Tablets

For conversion from parenteral morphine to Morphine Sulfate Tablets, anywhere from 3 to 6 mg of oral morphine sulfate may be required to provide pain relief equivalent to 1 mg of parenteral morphine.

Conversion from Other Opioids to Morphine Sulfate Tablets

There is inter-patient variability in the potency of opioid drugs and opioid formulations. Therefore, a conservative approach is advised when determining the total daily dosage of Morphine Sulfate Tablets. It is safer to underestimate a patient’s 24-hour Morphine Sulfate Tablets dosage than to overestimate the 24-hour Morphine Sulfate Tablets dosage and manage an adverse reaction due to overdose. Initiate dosing using Morphine Sulfate Tablets 15 mg to 30 mg mg every 4 hours.

Conversion from Morphine Sulfate Tablets to Extended-Release Morphine

For a given dose, the same total amount of morphine sulfate is available from Morphine Sulfate Tablets, and extended-release morphine formulations. The extended duration of release of morphine sulfate from extended-release formulations results in reduced maximum and increased minimum plasma morphine sulfate concentrations than with shorter acting morphine sulfate products. Conversion from Morphine Sulfate Tablets to the same total daily dose of an extended-release formulation could lead to excessive sedation at peak serum levels. Therefore, conversion to extended-release morphine formulations must be accompanied by close observation for signs of excessive sedation and respiratory depression.

2.3 Titration and Maintenance of Therapy

Individually titrate Morphine Sulfate Tablets to a dose that provides adequate analgesia and minimizes adverse reactions. Continually reevaluate patients receiving Morphine Sulfate Tablets to assess the maintenance of pain control and the relative incidence of adverse reactions, as well as monitoring for the development of addiction, abuse, or misuse [see Warnings and Precautions (5.1)]. Frequent communication is important among the prescriber, other members of the healthcare team, the patient, and the caregiver/family during periods of changing analgesic requirements, including initial titration.

If the level of pain increases after dosage stabilization, attempt to identify the source of increased pain before increasing the Morphine Sulfate Tablets dosage. If unacceptable opioid-related adverse reactions are observed, consider reducing the dosage. Adjust the dosage to obtain an appropriate balance between management of pain and opioid-related adverse reactions.

2.4 Discontinuation of Morphine Sulfate Tablets

When a patient who has been taking Morphine Sulfate Tablets regularly and may be physically dependent no longer requires therapy with Morphine Sulfate Tablets, taper the dose gradually, by 25% to 50% every 2 to 4 days, while monitoring carefully for signs and symptoms of withdrawal. If the patient develops these signs or symptoms, raise the dose to the previous level and taper more slowly, either by increasing the interval between dose decreases, decreasing the amount of change in dose, or both. Do not abruptly discontinue Morphine Sulfate Tablets in a physically-dependent patient [see Warnings and Precautions (5.12), Drug Abuse and Dependence (9.3)].

3 DOSAGE FORMS AND STRENGTHS

Each 15 mg tablet for oral administration contains: 15 mg morphine sulfate USP and is a white, biconvex tablet scored on one side and product identification "54" over "733" debossed on the other side.

Each 30 mg tablet for oral administration contains: 30 mg morphine sulfate USP and is a white, biconvex tablet scored on one side and product identification "54" over "262" debossed on the other side.

4 CONTRAINDICATIONS

Morphine Sulfate Tablets are contraindicated in patients with:

•
Significant respiratory depression [ see Warnings and Precautions (5.2)].
•
Acute or severe bronchial asthma in an unmonitored setting or in the absence of resuscitative equipment [ see Warnings and Precautions (5.5)].
•
Concurrent use of monoamine oxidase inhibitors (MAOIs) or use of MAOIs within the last 14 days [see Warnings and Precautions (5.6), Drug Interactions (7)].
•
Known or suspected gastrointestinal obstruction, including paralytic ileus [ see Warnings and Precautions (5.10)].

Hypersensitivity to morphine (e.g., anaphylaxis) [see Adverse Reactions (6)].

5 WARNINGS AND PRECAUTIONS

5.1 Addiction, Abuse, and Misuse

Morphine Sulfate Tablets contain morphine, a Schedule II controlled substance. As an opioid, Morphine Sulfate Tablets expose users to the risks of addiction, abuse, and misuse [see Drug Abuse and Dependence (9)].

Although the risk of addiction in any individual is unknown, it can occur in patients appropriately prescribed morphine sulfate. Addiction can occur at recommended dosages and if the drug is misused or abused.

Assess each patient’s risk for opioid addiction, abuse, or misuse prior to prescribing Morphine Sulfate Tablets, and monitor all patients receiving Morphine Sulfate Tablets for the development of these behaviors or conditions. Risks are increased in patients with a personal or family history of substance abuse (including drug or alcohol abuse or addiction) or mental illness (e.g., major depression). The potential for these risks should not, however, prevent the proper management of pain in any given patient. Patients at increased risk may be prescribed opioids such as Morphine Sulfate Tablets, but use in such patients necessitates intensive counseling about the risks and proper use of Morphine Sulfate Tablets along with intensive monitoring for signs of addiction, abuse, and misuse.

Opioids are sought by drug abusers and people with addiction disorders and are subject to criminal diversion. Consider these risks when prescribing or dispensing Morphine Sulfate Tablets. Strategies to reduce these risks include prescribing the drug in the smallest appropriate quantity and advising the patient on the proper disposal of unused drug [see Patient Counseling Information (17)]. Contact local state professional licensing board or state controlled substances authority for information on how to prevent and detect abuse or diversion of this product.

5.2 Life-Threatening Respiratory Depression

Serious, life-threatening, or fatal respiratory depression has been reported with the use of opioids, even when used as recommended. Respiratory depression, if not immediately recognized and treated, may lead to respiratory arrest and death. Management of respiratory depression may include close observation, supportive measures, and use of opioid antagonists, depending on the patient’s clinical status [see Overdosage (10)]. Carbon dioxide (CO2) retention from opioid-induced respiratory depression can exacerbate the sedating effects of opioids.

While serious, life-threatening, or fatal respiratory depression can occur at any time during the use of Morphine Sulfate Tablets, the risk is greatest during the initiation of therapy or following a dosage increase. Monitor patients closely for respiratory depression, especially within the first 24 to 72 hours of initiating therapy with and following dosage increases of Morphine Sulfate Tablets.

To reduce the risk of respiratory depression, proper dosing and titration of Morphine Sulfate Tablets are essential [see Dosage and Administration (2.2, 2.3)]. Overestimating the Morphine Sulfate Tablets dosage when converting patients from another opioid product can result in a fatal overdose with the first dose.

Accidental ingestion of even one dose of Morphine Sulfate Tablets, especially by children, can result in respiratory depression and death due to an overdose of morphine.

5.3 Neonatal Opioid Withdrawal Syndrome

Prolonged use of Morphine Sulfate Tablets during pregnancy can result in withdrawal in the neonate. Neonatal opioid withdrawal syndrome, unlike opioid withdrawal syndrome in adults, may be life-threatening if not recognized and treated, and requires management according to protocols developed by neonatology experts. Observe newborns for signs of neonatal opioid withdrawal syndrome and manage accordingly. Advise pregnant women using opioids for a prolonged period of the risk of neonatal opioid withdrawal syndrome and ensure that appropriate treatment will be available [see Use in Specific Populations (8.1), Patient Counseling Information (17)].

5.4 Risks from Concomitant Use with Benzodiazepines or Other CNS Depressants

Profound sedation, respiratory depression, coma, and death may result from the concomitant use of Morphine Sulfate Tablets with benzodiazepines or other CNS depressants (e.g., non-benzodiazepine sedatives/hypnotics, anxiolytics, tranquilizers, muscle relaxants, general anesthetics, antipsychotics, other opioids, alcohol). Because of these risks, reserve concomitant prescribing of these drugs for use in patients for whom alternative treatment options are inadequate.

Observational studies have demonstrated that concomitant use of opioid analgesics and benzodiazepines increases the risk of drug-related mortality compared to use of opioid analgesics alone. Because of similar pharmacological properties, it is reasonable to expect similar risk with the concomitant use of other CNS depressant drugs with opioid analgesics [see Drug Interactions (7)]. If the decision is made to prescribe a benzodiazepine or other CNS depressant concomitantly with an opioid analgesic, prescribe the lowest effective dosages and minimum durations of concomitant use. In patients already receiving an opioid analgesic, prescribe a lower initial dose of the benzodiazepine or other CNS depressant than indicated in the absence of an opioid, and titrate based on clinical response. If an opioid analgesic is initiated in a patient already taking a benzodiazepine or other CNS depressant, prescribe a lower initial dose of the opioid analgesic, and titrate based on clinical response. Follow patients closely for signs and symptoms of respiratory depression and sedation.

Advise both patients and caregivers about the risks of respiratory depression and sedation when Morphine Sulfate Tablets are used with benzodiazepines or other CNS depressants (including alcohol and illicit drugs). Advise patients not to drive or operate heavy machinery until the effects of concomitant use of the benzodiazepine or other CNS depressant have been determined. Screen patients for risk of substance use disorders, including opioid abuse and misuse, and warn them of the risk for overdose and death associated with the use of additional CNS depressants including alcohol and illicit drugs [see Drug Interactions (7), Patient Counseling Information (17)].

5.5 Life-Threatening Respiratory Depression in Patients with Chronic Pulmonary Disease or in Elderly, Cachectic, or Debilitated Patients

The use of Morphine Sulfate Tablets in patients with acute or severe bronchial asthma in an unmonitored setting or in the absence of resuscitative equipment is contraindicated.

Patients with Chronic Pulmonary Disease

Morphine Sulfate Tablets-treated patients with significant chronic obstructive pulmonary disease or cor pulmonale, and those with a substantially decreased respiratory reserve, hypoxia, hypercapnia, or pre-existing respiratory depression are at increased risk of decreased respiratory drive including apnea, even at recommended dosages of Morphine Sulfate Tablets [see Warnings and Precautions (5.2)].

Elderly, Cachectic, or Debilitated Patients

Life-threatening respiratory depression is more likely to occur in elderly, cachectic, or debilitated patients because they may have altered pharmacokinetics or altered clearance compared to younger, healthier patients [see Warnings and Precautions (5.2)].

Monitor such patients closely, particularly when initiating and titrating Morphine Sulfate Tablets and when Morphine Sulfate Tablets are given concomitantly with other drugs that depress respiration [see Warnings and Precautions (5.4)]. Alternatively, consider the use of non-opioid analgesics in these patients.

5.6 Interaction with Monoamine Oxidase Inhibitors

Monoamine oxidase inhibitors (MAOIs) may potentiate the effects of morphine, including respiratory depression, coma, and confusion. Morphine Sulfate Tablets should not be used in patients taking MAOIs or within 14 days of stopping such treatment.

5.7 Adrenal Insufficiency

Cases of adrenal insufficiency have been reported with opioid use, more often following greater than one month of use. Presentation of adrenal insufficiency may include non-specific symptoms and signs including nausea, vomiting, anorexia, fatigue, weakness, dizziness, and low blood pressure. If adrenal insufficiency is suspected, confirm the diagnosis with diagnostic testing as soon as possible. If adrenal insufficiency is diagnosed, treat with physiologic replacement doses of corticosteroids. Wean the patient off of the opioid to allow adrenal function to recover and continue corticosteroid treatment until adrenal function recovers. Other opioids may be tried as some cases reported use of a different opioid without recurrence of adrenal insufficiency. The information available does not identify any particular opioids as being more likely to be associated with adrenal insufficiency.

5.8 Severe Hypotension

Morphine Sulfate Tablets may cause severe hypotension including orthostatic hypotension and syncope in ambulatory patients. There is increased risk in patients whose ability to maintain blood pressure has already been compromised by a reduced blood volume or concurrent administration of certain CNS depressant drugs (e.g., phenothiazines or general anesthetics) [see Drug Interactions (7)]. Monitor these patients for signs of hypotension after initiating or titrating the dosage of Morphine Sulfate Tablets. In patients with circulatory shock, Morphine Sulfate Tablets may cause vasodilation that can further reduce cardiac output and blood pressure. Avoid the use of Morphine Sulfate Tablets in patients with circulatory shock.

5.9 Risks of Use in Patients with Increased Intracranial Pressure, Brain Tumors, Head Injury, or Impaired Consciousness

In patients who may be susceptible to the intracranial effects of CO2 retention (e.g., those with evidence of increased intracranial pressure or brain tumors), Morphine Sulfate Tablets may reduce respiratory drive, and the resultant CO2 retention can further increase intracranial pressure. Monitor such patients for signs of sedation and respiratory depression, particularly when initiating therapy with Morphine Sulfate Tablets.

Opioids may also obscure the clinical course in a patient with a head injury. Avoid the use of Morphine Sulfate Tablets in patients with impaired consciousness or coma.

5.10 Risks of Use in Patients with Gastrointestinal Conditions

Morphine Sulfate Tablets are contraindicated in patients with gastrointestinal obstruction, including paralytic ileus.

The morphine in Morphine Sulfate Tablets may cause spasm of the sphincter of Oddi. Opioids may cause increases in serum amylase. Monitor patients with biliary tract disease, including acute pancreatitis for worsening symptoms.

5.11 Increased Risk of Seizures in Patients with Seizure Disorders

The morphine in Morphine Sulfate Tablets may increase the frequency of seizures in patients with seizure disorders, and may increase the risk of seizures occurring in other clinical settings associated with seizures. Monitor patients with a history of seizure disorders for worsened seizure control during Morphine Sulfate Tablets therapy.

5.12 Withdrawal

Avoid the use of mixed agonist/antagonist (e.g., pentazocine, nalbuphine, and butorphanol) or partial agonist (e.g., buprenorphine) analgesics in patients who are receiving a full opioid agonist analgesic, including Morphine Sulfate Tablets. In these patients, mixed agonist/antagonist and partial agonist analgesics may reduce the analgesic effect and/or precipitate withdrawal symptoms.

When discontinuing Morphine Sulfate Tablets, gradually taper the dosage [see Dosage and Administration (2.4)]. Do not abruptly discontinue Morphine Sulfate Tablets [see Drug Abuse and Dependence (9.3)].

5.13 Risks of Driving and Operating Machinery

Morphine Sulfate Tablets may impair the mental or physical abilities needed to perform potentially hazardous activities such as driving a car or operating machinery. Warn patients not to drive or operate dangerous machinery unless they are tolerant to the effects of Morphine Sulfate Tablets and know how they will react to the medication [see Patient Counseling Information (17)].

6 ADVERSE REACTIONS

The following serious adverse reactions are described, or described in greater detail, in other sections:

•
Addiction, Abuse, and Misuse [ see Warnings and Precautions (5.1)]
•
Life-Threatening Respiratory Depression [ see Warnings and Precautions (5.2)]
•
Neonatal Opioid Withdrawal Syndrome [ see Warnings and Precautions (5.3)]
•
Interactions with Benzodiazepine or Other CNS Depressants [ see Warnings and Precautions (5.4)]
•
Adrenal Insufficiency [ see Warnings and Precautions (5.7)]
•
Severe Hypotension [ see Warnings and Precautions (5.8)]
•
Gastrointestinal Adverse Reactions [ see Warnings and Precautions (5.10)]
•
Seizures [ see Warnings and Precautions (5.11)]
•
Withdrawal [ see Warnings and Precautions (5.12)]

The following adverse reactions associated with the use of morphine were identified in clinical studies or postmarketing reports. Because some of these reactions were reported voluntarily from a population of uncertain size, it is not always possible to reliably estimate their frequency or establish a causal relationship to drug exposure.

Serious adverse reactions associated with morphine use included: respiratory depression, apnea, and to a lesser degree, circulatory depression, respiratory arrest, shock and cardiac arrest.

The common adverse reactions seen on initiation of therapy with morphine were dose-dependent and were typical opioid-related adverse reactions. The most frequent of these included: constipation, nausea, and somnolence. Other commonly observed adverse reactions included: lightheadedness, dizziness, sedation, vomiting, and sweating. The frequency of these events depended upon several factors including clinical setting, the patient’s level of opioid tolerance, and host factors specific to the individual.

Other less frequently observed adverse reactions from opioid analgesics, including morphine sulfate included:

Body as a Whole: malaise, withdrawal syndrome

Cardiovascular System: bradycardia, hypertension, hypotension, palpitations, syncope, tachycardia

Digestive System: biliary pain, dyspepsia, dysphagia, gastroenteritis, abnormal liver function tests, rectal disorder, thirst

Endocrine: hypogonadism

Hemic and Lymphatic System: anemia, thrombocytopenia

Metabolic and Nutritional Disorders: edema, weight loss

Musculoskeletal: skeletal muscle rigidity, decreased bone mineral density

Nervous System: abnormal dreams, abnormal gait, agitation, amnesia, anxiety, ataxia, confusion, convulsions, coma, delirium, depression, dry mouth, euphoria, hallucinations, lethargy, nervousness, abnormal thinking, tremor, vasodilation, vertigo, headache

Respiratory System: hiccup, hypoventilation, voice alteration

Skin and Appendages: dry skin, urticaria, pruritus

Special Senses: amblyopia, eye pain, taste perversion

Urogenital System: abnormal ejaculation, dysuria, impotence, decreased libido, oliguria, urinary retention or hesitancy, anti-diuretic effect, amenorrhea

Serotonin Syndrome: Cases of serotonin syndrome, a potentially life-threatening condition, have been reported during concomitant use of opioids with serotonergic drugs.

Adrenal Insufficiency: Cases of adrenal insufficiency have been reported with opioid use, more often following greater than one month of use.

Anaphylaxis: Anaphylaxis has been reported with ingredients contained in Morphine Sulfate Tablets.

Androgen Deficiency: Cases of androgen deficiency have occurred with chronic use of opioids [see Clinical Pharmacology (12.2)].

7 DRUG INTERACTIONS

Table 1 includes clinically significant drug interactions with Morphine Sulfate Tablets.

Table 1: Clinically Significant Drug Interactions with Morphine Sulfate Tablets

Benzodiazepines and Central Nervous System (CNS) Depressants

Clinical Impact:

Due to additive pharmacologic effect, the concomitant use of benzodiazepines or other CNS depressants, including alcohol, can increase the risk of hypotension, respiratory depression, profound sedation, coma, and death.

Intervention:

Reserve concomitant prescribing of these drugs for use in patients for whom alternative treatment options are inadequate. Limit dosages and durations to the minimum required. Follow patients closely for signs of respiratory depression and sedation [see Warnings and Precautions (5.4)].

Examples:

Benzodiazepines and other sedatives/hypnotics, anxiolytics, tranquilizers, muscle relaxants, general anesthetics, antipsychotics, other opioids, alcohol.

Serotonergic Drugs

Clinical Impact:

The concomitant use of opioids with other drugs that affect the serotonergic neurotransmitter system has resulted in serotonin syndrome.

Intervention:

If concomitant use is warranted, carefully observe the patient, particularly during treatment initiation and dose adjustment. Discontinue Morphine Sulfate Tablets if serotonin syndrome is suspected.

Examples:

Selective serotonin reuptake inhibitors (SSRIs), serotonin and norepinephrine reuptake inhibitors (SNRIs), tricyclic antidepressants (TCAs), triptans, 5-HT3 receptor antagonists, drugs that effect the serotonin neurotransmitter system (e.g., mirtazapine, trazodone, tramadol), monoamine oxidase (MAO) inhibitors (those intended to treat psychiatric disorders and also others, such as linezolid and intravenous methylene blue).

Monoamine Oxidase Inhibitors (MAOIs)

Clinical Impact:

MAOI interactions with opioids may manifest as serotonin syndrome or opioid toxicity (e.g., respiratory depression, coma) [see Warnings and Precautions (5.6)].

Intervention:

Do not use Morphine Sulfate Tablets in patients taking MAOIs or within 14 days of stopping such treatment.

Examples:

Phenelzine, tranylcypromine, linezolid.

Mixed Agonist/Antagonist and Partial Agonist Opioid Analgesics

Clinical Impact:

May reduce the analgesic effect of Morphine Sulfate Tablets and/or precipitate withdrawal symptoms.

Intervention:

Avoid concomitant use.

Examples:

Butorphanol, nalbuphine, pentazocine, buprenorphine.

Muscle Relaxants

Clinical Impact:

Morphine may enhance the neuromuscular blocking action of skeletal muscle relaxants and produce an increased degree of respiratory depression.

Intervention:

Monitor patients for signs of respiratory depression that may be greater than otherwise expected and decrease the dosage of Morphine Sulfate Tablets and/or the muscle relaxant as necessary.

Cimetidine

Clinical Impact:

The concomitant use of morphine and cimetidine has been reported to precipitate apnea, confusion, and muscle twitching in an isolated report.

Intervention:

Monitor patients for increased respiratory and CNS depression when Morphine Sulfate Tablets are used concomitantly with cimetidine.

Diuretics

Clinical Impact:

Opioids can reduce the efficacy of diuretics by inducing the release of antidiuretic hormone.

Intervention:

Monitor patients for signs of diminished diuresis and/or effects on blood pressure and increase the dosage of the diuretic as needed.

Anticholinergic Drugs

Clinical Impact:

The concomitant use of anticholinergic drugs may increase risk of urinary retention and/or severe constipation, which may lead to paralytic ileus.

Intervention:

Monitor patients for signs of urinary retention or reduced gastric motility when Morphine Sulfate Tablets are used concomitantly with anticholinergic drugs.

P-Glycoprotein (P-gp) Inhibitors

Clinical Impact:

The concomitant use of P-gp inhibitors can increase the exposure to morphine by two-fold and can increase the risk of hypotension, respiratory depression, profound sedation, coma, and death.

Intervention:

Monitor patients for signs of respiratory depression that may be greater than otherwise expected and decrease the dosage of Morphine Sulfate Tablets and/or the P-gp inhibitor as necessary.

Examples:

Quinidine, verapamil.

8 USE IN SPECIFIC POPULATIONS

8.1 Pregnancy

Risk Summary

Prolonged use of opioid analgesics during pregnancy can cause neonatal opioid withdrawal syndrome [see Warnings and Precautions (5.3)]. There are no available data with Morphine Sulfate Tablets in pregnant women to inform a drug-associated risk for major birth defects and miscarriage. Published studies with morphine use during pregnancy have not reported a clear association with morphine and major birth defects [see Human Data]. In published animal reproduction studies, morphine administered subcutaneously during the early gestational period produced neural tube defects (i.e., exencephaly and cranioschisis) at 5 and 16 times the human daily dose of 60 mg based on body surface area (HDD) in hamsters and mice, respectively, lower fetal body weight and increased incidence of abortion at 0.4 times the HDD in the rabbit, growth retardation at 6 times the HDD in the rat, and axial skeletal fusion and cryptorchidism at 16 times the HDD in the mouse. Administration of morphine sulfate to pregnant rats during organogenesis and through lactation resulted in cyanosis, hypothermia, decreased brain weights, pup mortality, decreased pup body weights, and adverse effects on reproductive tissues at 3 to 4 times the HDD; and long-term neurochemical changes in the brain of offspring which correlate with altered behavioral responses that persist through adulthood at exposures comparable to and less than the HDD [see Animal Data].Based on animal data, advise pregnant women of the potential risk to a fetus.

The estimated background risk of major birth defects and miscarriage for the indicated population is unknown. All pregnancies have a background risk of birth defect, loss, or other adverse outcomes. In the U.S. general population, the estimated background risk of major birth defects and miscarriage in clinically recognized pregnancies is 2% to 4% and 15% to 20%, respectively.

Clinical Considerations

Fetal/Neonatal Adverse Reactions: Prolonged use of opioid analgesics during pregnancy for medical or nonmedical purposes can result in physical dependence in the neonate and neonatal opioid withdrawal syndrome shortly after birth. Neonatal opioid withdrawal syndrome presents as irritability, hyperactivity and abnormal sleep pattern, high pitched cry, tremor, vomiting, diarrhea, and failure to gain weight. The onset, duration, and severity of neonatal withdrawal syndrome vary based on the specific opioid used, duration of use, timing and amount of last maternal use, and rate of elimination of the drug by the newborn. Observe newborns for signs of neonatal opioid withdrawal syndrome and manage accordingly [see Warnings and Precautions (5.3)].

Labor or Delivery: Opioids cross the placenta and may produce respiratory depression and psycho-physiologic effects in neonates. An opioid antagonist, such as naloxone, must be available for reversal of opioid induced respiratory depression in the neonate. Morphine Sulfate Tablets are not recommended for use in women during and immediately prior to labor, when use of shorter-acting analgesics or other analgesic techniques are more appropriate. Opioid analgesics, including Morphine Sulfate Tablets, can prolong labor through actions that temporarily reduce the strength, duration, and frequency of uterine contractions. However, this effect is not consistent and may be offset by an increased rate of cervical dilatation, which tends to shorten labor. Monitor neonates exposed to opioid analgesics during labor for signs of excess sedation and respiratory depression.

Data

Human Data: The results from a population-based prospective cohort, including 70 women exposed to morphine during the first trimester of pregnancy and 448 women exposed to morphine at any time during pregnancy, indicate no increased risk for congenital malformations. However, these studies cannot definitely establish the absence of any risk because of methodological limitations, including small sample size and non-randomized study design.

Animal Data: Formal reproductive and developmental toxicology studies for morphine have not been conducted. Exposure margins for the following published study reports are based on human daily dose of 60 mg morphine using a body surface area comparison (HDD).

Neural tube defects (exencephaly and cranioschisis) were noted following subcutaneous administration of morphine sulfate (35 to 322 mg/kg) on Gestation Day 8 to pregnant hamsters (4.7 to 43.5 times the HDD). A no adverse effect level was not defined in this study and the findings cannot be clearly attributed to maternal toxicity. Neural tube defects (exencephaly), axial skeletal fusions, and cryptorchidism were reported following a single subcutaneous (SC) injection of morphine sulfate to pregnant mice (100 to 500 mg/kg) on Gestation Day 8 or 9 at 200 mg/kg or greater (16 times the HDD) and fetal resorption at 400 mg/kg or higher (32 times the HDD). No adverse effects were noted following 100 mg/kg morphine in this model (8 times the HDD). In one study, following continuous subcutaneous infusion of doses greater than or equal to 2.72 mg/kg to mice (0.2 times the HDD), exencephaly, hydronephrosis, intestinal hemorrhage, split supraoccipital, malformed sternebrae, and malformed xiphoid were noted. The effects were reduced with increasing daily dose; possibly due to rapid induction of tolerance under these infusion conditions. The clinical significance of this report is not clear.

Decreased fetal weights were observed in pregnant rats treated with 20 mg/kg/day morphine sulfate (3.2 times the HDD) from Gestation Day 7 to 9. There was no evidence of malformations despite maternal toxicity (10% mortality). In a second rat study, decreased fetal weight and increased incidences of growth retardation were noted at 35 mg/kg/day (5.7 times the HDD) and there was a reduced number of fetuses at 70 mg/kg/day (11.4 times the HDD) when pregnant rats were treated with 10, 35, or 70 mg/kg/day morphine sulfate via continuous infusion from Gestation Day 5 to 20. There was no evidence of fetal malformations or maternal toxicity.

An increased incidence of abortion was noted in a study in which pregnant rabbits were treated with 2.5 (0.8 times the HDD) to 10 mg/kg morphine sulfate via subcutaneous injection from Gestation Day 6 to 10. In a second study, decreased fetal body weights were reported following treatment of pregnant rabbits with increasing doses of morphine (10 to 50 mg/kg/day) during the pre-mating period and 50 mg/kg/day (16 times the HDD) throughout the gestation period. No overt malformations were reported in either publication; although only limited endpoints were evaluated.

In published studies in rats, exposure to morphine during gestation and/or lactation periods is associated with: decreased pup viability at 12.5 mg/kg/day or greater (2 times the HDD); decreased pup body weights at 15 mg/kg/day or greater (2.4 times the HDD); decreased litter size, decreased absolute brain and cerebellar weights, cyanosis, and hypothermia at 20 mg/kg/day (3.2 times the HDD); alteration of behavioral responses (play, social-interaction) at 1 mg/kg/day or greater (0.2 times the HDD); alteration of maternal behaviors (e.g., decreased nursing and pup retrievals) in mice at 1 mg/kg or higher (0.08 times the HDD) and rats at 1.5 mg/kg/day or higher (0.2 times the HDD); and a host of behavioral abnormalities in the offspring of rats, including altered responsiveness to opioids at 4 mg/kg/day (0.7 times the HDD) or greater.

Fetal and/or postnatal exposure to morphine in mice and rats has been shown to result in morphological changes in fetal and neonatal brain and neuronal cell loss, alteration of a number of neurotransmitter and neuromodulator systems, including opioid and non-opioid systems, and impairment in various learning and memory tests that appear to persist into adulthood. These studies were conducted with morphine treatment usually in the range of 4 to 20 mg/kg/day (0.7 to 3.2 times the HDD).

Additionally, delayed sexual maturation and decreased sexual behaviors in female offspring at 20 mg/kg/day (3.2 times the HDD), and decreased plasma and testicular levels of luteinizing hormone and testosterone, decreased testes weights, seminiferous tubule shrinkage, germinal cell aplasia, and decreased spermatogenesis in male offspring were also observed at 20 mg/kg/day (3.2 times the HDD). Decreased litter size and viability were observed in the offspring of male rats that were intraperitoneally administered morphine sulfate for 1 day prior to mating at 25 mg/kg/day (4.1 times the HDD) and mated to untreated females. Decreased viability and body weight and/or movement deficits in both first and second generation offspring were reported when male mice were treated for 5 days with escalating doses of 120 to 240 mg/kg/day morphine sulfate (9.7 to 19.5 times the HDD) or when female mice treated with escalating doses of 60 to 240 mg/kg/day (4.9 to 19.5 times the HDD) followed by a 5-day treatment-free recovery period prior to mating. Similar multigenerational findings were also seen in female rats pre-gestationally treated with escalating doses of 10 to 22 mg/kg/day morphine (1.6 to 3.6 times the HDD).

8.2 Lactation

Risk Summary

Morphine is present in breast milk. Published lactation studies report variable concentrations of morphine in breast milk with administration of immediate-release morphine to nursing mothers in the early postpartum period with a milk-to-plasma morphine AUC ratio of 2.5:1 measured in one lactation study. However, there is insufficient information to determine the effects of morphine on the breastfed infant and the effects of morphine on milk production. Lactation studies have not been conducted with Morphine Sulfate Tablets and no information is available on the effects of the drug on the breastfed infant or the effects of the drug on milk production.

The developmental and health benefits of breastfeeding should be considered along with the mother’s clinical need for Morphine Sulfate Tablets and any potential adverse effects on the breastfed infant from Morphine Sulfate Tablets or from the underlying maternal condition.

Clinical Considerations

Monitor infants exposed to Morphine Sulfate Tablets through breast milk for excess sedation and respiratory depression. Withdrawal symptoms can occur in breastfed infants when maternal administration of morphine is stopped, or when breastfeeding is stopped.

8.3 Females and Males of Reproductive Potential

Infertility

Chronic use of opioids may cause reduced fertility in females and males of reproductive potential. It is not known whether these effects on fertility are reversible [see Adverse Reactions (6), Clinical Pharmacology (12.2)].

In published animal studies, morphine administration adversely effected fertility and reproductive endpoints in male rats and prolonged estrus cycle in female rats [see Nonclinical Toxicology (13)].

8.4 Pediatric Use

The safety and effectiveness and the pharmacokinetics of Morphine Sulfate Tablets in pediatric patients below the age of 18 have not been established.

8.5 Geriatric Use

Elderly patients (aged 65 years or older) may have increased sensitivity to morphine. In general, use caution when selecting a dose for an elderly patient, usually starting at the low end of the dosing range, reflecting the greater frequency of decreased hepatic, renal, or cardiac function and of concomitant disease or other drug therapy.

Respiratory depression is the chief risk for elderly patients treated with opioids, and has occurred after large initial doses were administered to patients who were not opioid-tolerant or when opioids were co-administered with other agents that depress respiration. Titrate the dosage of Morphine Sulfate Tablets slowly in geriatric patients and monitor closely for signs of respiratory depression [see Warnings and Precautions (5.5)]. Morphine is known to be substantially excreted by the kidney, and the risk of adverse reactions to this drug may be greater in patients with impaired renal function. Because elderly patients are more likely to have decreased renal function, care should be taken in dose selection, and it may be useful to monitor renal function.

8.6 Hepatic Impairment

Morphine pharmacokinetics have been reported to be significantly altered in patients with cirrhosis. Start these patients with a lower than usual dosage of Morphine Sulfate Tablets and titrate slowly while monitoring for signs of respiratory depression, sedation, and hypotension [see Clinical Pharmacology (12.3)].

8.7 Renal Impairment

Morphine sulfate pharmacokinetics are altered in patients with renal failure. Start these patients with a lower than usual dosage of Morphine Sulfate Tablets and titrate slowly while monitoring for signs of respiratory depression, sedation, and hypotension [see Clinical Pharmacology (12.3)].

9 DRUG ABUSE AND DEPENDENCE

9.1 Controlled Substance

Morphine Sulfate Tablets contain morphine, a Schedule II controlled substance.

9.2 Abuse

Morphine Sulfate Tablets contains morphine, a substance with a high potential for abuse similar to other opioids including fentanyl, hydrocodone, hydromorphone, methadone, oxycodone, oxymorphone, and tapentadol. Morphine Sulfate Tablets can be abused and are subject to misuse, addiction, and criminal diversion [see Warnings and Precautions (5.1)].

All patients treated with opioids require careful monitoring for signs of abuse and addiction, because use of opioid analgesic products carry the risk of addiction even under appropriate medical use.

Prescription drug abuse is the intentional non-therapeutic use of a prescription drug, even once, for its rewarding psychological or physiological effects.

Drug addiction is a cluster of behavioral, cognitive, and physiological phenomena that develop after repeated substance use and includes: a strong desire to take the drug, difficulties in controlling its use, persisting in its use despite harmful consequences, a higher priority given to drug use than to other activities and obligations, increased tolerance, and sometimes a physical withdrawal.

“Drug-seeking” behavior is very common in persons with substance use disorders. Drug-seeking tactics include emergency calls or visits near the end of office hours, refusal to undergo appropriate examination, testing, or referral, repeated “loss” of prescriptions, tampering with prescriptions and reluctance to provide prior medical records or contact information for other treating health care provider(s). “Doctor shopping” (visiting multiple prescribers to obtain additional prescriptions) is common among drug abusers and people suffering from untreated addiction. Preoccupation with achieving adequate pain relief can be appropriate behavior in a patient with poor pain control.

Abuse and addiction are separate and distinct from physical dependence and tolerance. Healthcare providers should be aware that addiction may not be accompanied by concurrent tolerance and symptoms of physical dependence in all addicts. In addition, abuse of opioids can occur in the absence of true addiction.

Morphine Sulfate Tablets, like other opioids, can be diverted for non-medical use into illicit channels of distribution. Careful record-keeping of prescribing information, including quantity, frequency, and renewal requests, as required by state and federal law, is strongly advised.

Proper assessment of the patient, proper prescribing practices, periodic re-evaluation of therapy, and proper dispensing and storage are appropriate measures that help to limit abuse of opioid drugs.

Risks Specific to Abuse of Morphine Sulfate Tablets

Morphine Sulfate Tablets are for oral use only. Abuse of Morphine Sulfate Tablets poses a risk of overdose and death. The risk is increased with concurrent abuse of Morphine Sulfate Tablets with alcohol and other central nervous system depressants. Parenteral drug abuse is commonly associated with transmission of infectious diseases such as hepatitis and HIV.

9.3 Dependence

Both tolerance and physical dependence can develop during chronic opioid therapy. Tolerance is the need for increasing doses of opioids to maintain a defined effect such as analgesia (in the absence of disease progression or other external factors). Tolerance may occur to both the desired and undesired effects of drugs, and may develop at different rates for different effects.

Physical dependence results in withdrawal symptoms after abrupt discontinuation or a significant dosage reduction of a drug. Withdrawal also may be precipitated through the administration of drugs with opioid antagonist activity (e.g., naloxone, nalmefene), mixed agonist/antagonist analgesics (e.g., pentazocine, butorphanol, nalbuphine), or partial agonists (e.g., buprenorphine). Physical dependence may not occur to a clinically significant degree until after several days to weeks of continued opioid usage.

Morphine Sulfate Tablets should not be abruptly discontinued in a physically-dependent patient [see Dosage and Administration (2.4)]. If Morphine Sulfate Tablets are abruptly discontinued in a physically-dependent patient, a withdrawal syndrome may occur. Some or all of the following can characterize this syndrome: restlessness, lacrimation, rhinorrhea, yawning, perspiration, chills, myalgia, and mydriasis. Other signs and symptoms also may develop, including: irritability, anxiety, backache, joint pain, weakness, abdominal cramps, insomnia, nausea, anorexia, vomiting, diarrhea, or increased blood pressure, respiratory rate, or heart rate.

Infants born to mothers physically dependent on opioids will also be physically dependent and may exhibit respiratory difficulties and withdrawal signs [see Use in Specific Populations (8.1)].

10 OVERDOSAGE

Clinical Presentation

Acute overdose with Morphine Sulfate Tablets can be manifested by respiratory depression, somnolence progressing to stupor or coma, skeletal muscle flaccidity, cold and clammy skin, constricted pupils, and, in some cases, pulmonary edema, bradycardia, hypotension, partial or complete airway obstruction, atypical snoring, and death. Marked mydriasis rather than miosis may be seen with hypoxia in overdose situations [see Clinical Pharmacology (12.2)].

Treatment of Overdose

In case of overdose, priorities are the reestablishment of a patent and protected airway and institution of assisted or controlled ventilation, if needed. Employ other supportive measures (including oxygen and vasopressors) in the management of circulatory shock and pulmonary edema as indicated. Cardiac arrest or arrhythmias will require advanced life-support techniques.

The opioid antagonists, naloxone or nalmefene, are specific antidotes to respiratory depression resulting from opioid overdose. For clinically significant respiratory or circulatory depression secondary to morphine overdose, administer an opioid antagonist. Opioid antagonists should not be administered in the absence of clinically significant respiratory or circulatory depression secondary to morphine overdose.

Because the duration of opioid reversal is expected to be less than the duration of action of morphine in Morphine Sulfate Tablets, carefully monitor the patient until spontaneous respiration is reliably reestablished. If the response to an opioid antagonist is suboptimal or only brief in nature, administer additional antagonist as directed by the product’s prescribing information.

In an individual physically dependent on opioids, administration of the recommended usual dosage of the antagonist will precipitate an acute withdrawal syndrome. The severity of the withdrawal symptoms experienced will depend on the degree of physical dependence and the dose of the antagonist administered. If a decision is made to treat serious respiratory depression in the physically dependent patient, administration of the antagonist should be initiated with care and by titration with smaller than usual doses of the antagonist.

11 DESCRIPTION

Morphine Sulfate Tablets are an opioid agonist, available in 15 mg and 30 mg for oral administration. Chemically, morphine sulfate is 7,8-didehydro-4,5 alpha-epoxy-17 methylmorphinan-3,6 alpha-diol sulfate (2:1) (salt) pentahydrate. Morphine sulfate USP is a white to off-white crystalline powder or a fine white to light yellow powder. It is soluble in water and slightly soluble in alcohol, but is practically insoluble in chloroform or ether. The octanol:water partition coefficient of morphine is 1.42 at physiologic pH and the pka is 7.9 for the tertiary nitrogen (the majority is ionized at pH 7.4). Its molecular formula is (C17H19NO3)2 • H2SO4 • 5H2O, and it has the following chemical structure:

Each tablet contains 15 or 30 mg of morphine sulfate USP and the following inactive ingredients: colloidal silicon dioxide, corn starch, microcrystalline cellulose, pregelatinized starch and stearic acid.

12 CLINICAL PHARMACOLOGY

12.1 Mechanism of Action

Morphine is a full opioid agonist and is relatively selective for the mu-opioid receptor, although it can bind to other opioid receptors at higher doses. The principal therapeutic action of morphine is analgesia. Like all full opioid agonists, there is no ceiling effect for analgesia with morphine. Clinically, dosage is titrated to provide adequate analgesia and may be limited by adverse reactions, including respiratory and CNS depression.

The precise mechanism of the analgesic action is unknown. However, specific CNS opioid receptors for endogenous compounds with opioid-like activity have been identified throughout the brain and spinal cord and are thought to play a role in the analgesic effects of this drug.

12.2 Pharmacodynamics

Effects on the Central Nervous System

Morphine produces respiratory depression by direct action on brain stem respiratory centers. The respiratory depression involves a reduction in the responsiveness of the brain stem respiratory centers to both increases in carbon dioxide tension and electrical stimulation.

Morphine causes miosis, even in total darkness. Pinpoint pupils are a sign of opioid overdose but are not pathognomonic (e.g., pontine lesions of hemorrhagic or ischemic origins may produce similar findings). Marked mydriasis rather than miosis may be seen due to hypoxia in overdose situations.

Effects on the Gastrointestinal Tract and Other Smooth Muscle

Morphine causes a reduction in motility associated with an increase in smooth muscle tone in the antrum of the stomach and duodenum. Digestion of food in the small intestine is delayed and propulsive contractions are decreased. Propulsive peristaltic waves in the colon are decreased, while tone may be increased to the point of spasm, resulting in constipation. Other opioid-induced effects may include a reduction in biliary and pancreatic secretions, spasm of sphincter of Oddi, and transient elevations in serum amylase.

Effects on the Cardiovascular System

Morphine produces peripheral vasodilation which may result in orthostatic hypotension or syncope. Manifestations of histamine release and/or peripheral vasodilation may include pruritus, flushing, red eyes, sweating, and/or orthostatic hypotension.

Effects on the Endocrine System

Opioids inhibit the secretion of adrenocorticotropic hormone (ACTH), cortisol, and luteinizing hormone (LH) in humans [see Adverse Reactions (6)]. They also stimulate prolactin, growth hormone (GH) secretion, and pancreatic secretion of insulin and glucagon.

Chronic use of opioids may influence the hypothalamic-pituitary-gonadal axis, leading to androgen deficiency that may manifest as low libido, impotence, erectile dysfunction, amenorrhea, or infertility. The causal role of opioids in the clinical syndrome of hypogonadism is unknown because the various medical, physical, lifestyle, and psychological stressors that may influence gonadal hormone levels have not been adequately controlled for in studies conducted to date [see Adverse Reactions (6)].

Effects on the Immune System

Opioids have been shown to have a variety of effects on components of the immune system in in vitro and animal models. The clinical significance of these findings is unknown. Overall, the effects of opioids appear to be modestly immunosuppressive.

Concentration–Efficacy Relationships

The minimum effective analgesic concentration will vary widely among patients, especially among patients who have been previously treated with potent agonist opioids. The minimum effective analgesic concentration of morphine for any individual patient may increase over time due to an increase in pain, the development of a new pain syndrome and/or the development of analgesic tolerance [see Dosage and Administration (2.1, 2.2)].

Concentration–Adverse Reaction Relationships

There is a relationship between increasing morphine plasma concentration and increasing frequency of dose-related opioid adverse reactions such as nausea, vomiting, CNS effects, and respiratory depression. In opioid-tolerant patients, the situation may be altered by the development of tolerance to opioid-related adverse reactions [see Dosage and Administration (2.1, 2.2, 2.3)].

12.3 Pharmacokinetics

Absorption

Morphine, when administered as morphine sulfate is about two-thirds absorbed from the gastrointestinal tract with the maximum analgesic effect occurring 60 minutes post-administration. The oral bioavailability of morphine sulfate is less than 40% and shows large inter-individual variability due to extensive pre-systemic metabolism.

Administration of the 30 mg Morphine Sulfate Tablet and 30 mg of Morphine Sulfate Oral Solution every six hours for 5 days resulted in a comparable 24-hour exposure (AUC). The steady-state levels were achieved within 48 hours for both tablets and solution. The mean steady state Cmax values were about 78 and 58 ng/mL for tablets and solution, respectively.

Food Effects: When morphine sulfate 30 mg tablet was administered 30 minutes after ingesting a high fat/high calorie meal, there was no change in the extent of absorption (AUC) of morphine sulfate. There was, however, an increase in the median Tmax from 0.5 to 0.75 hours and an 11% decrease in Cmax. The tablet can be administered without regard to meals.

Distribution

Once absorbed, morphine sulfate is distributed to skeletal muscle, kidneys, liver, intestinal tract, lungs, spleen and brain. Although the primary site of action is the CNS, only small quantities cross the blood-brain barrier. Morphine sulfate also crosses the placental membranes and has been found in breast milk. The volume of distribution of morphine sulfate is approximately 1 to 6 L/kg, and morphine sulfate is 20% to 35% reversibly bound to plasma proteins.

Elimination

Metabolism: The major pathway of morphine sulfate detoxification is conjugation, either with D-glucuronic acid to produce glucuronides or with sulfuric acid to produce morphine-3-etheral sulfate. While a small fraction (less than 5%) of morphine sulfate is demethylated, virtually all morphine sulfate is converted by hepatic metabolism to the 3- and 6-glucuronide metabolites (M3G and M6G; about 50% and 15%, respectively). M6G has been shown to have analgesic activity but crosses the blood-brain barrier poorly, while M3G has no significant analgesic activity.

Excretion: Most of a dose of morphine sulfate is excreted in urine as M3G and M6G, with elimination of morphine sulfate occurring primarily as renal excretion of M3G. Approximately 10% of the dose is excreted unchanged in urine. A small amount of glucuronide conjugates are excreted in bile, with minor enterohepatic recycling. Seven to 10% of administered morphine sulfate is excreted in the feces.

The mean adult plasma clearance is approximately 20 to 30 mL/min/kg. The effective terminal half-life of morphine sulfate after IV administration is reported to be approximately 2 hours. In some studies involving longer periods of plasma sampling, a longer terminal half-life of morphine sulfate of about 15 hours was reported.

Specific Populations

Race/ Ethnicity: There may be some pharmacokinetic differences associated with race. In one published study, Chinese subjects given intravenous morphine sulfate had a higher clearance when compared to Caucasian subjects (1852 +/- 116 mL/min compared to 1495 +/- 80 mL/min).

Sex: While evidence of greater post-operative morphine sulfate consumption in men compared to women is present in the literature, clinically significant differences in analgesic outcomes and pharmacokinetic parameters have not been consistently demonstrated. Some studies have shown an increased sensitivity to the adverse effects of morphine sulfate, including respiratory depression, in women compared to men.

Hepatic Impairment: Morphine pharmacokinetics are altered in patients with cirrhosis. Clearance was found to decrease with a corresponding increase in half-life. The M3G and M6G to morphine AUC ratios also decreased in these subjects, indicating diminished metabolic activity. Adequate studies of the pharmacokinetics of morphine in patients with severe hepatic impairment have not been conducted.

Renal Impairment: Morphine pharmacokinetics are altered in patients with renal failure. The AUC is increased and clearance is decreased and the metabolites, M3G and M6G, may accumulate to much higher plasma levels in patients with renal failure as compared to patients with normal renal function. Adequate studies of the pharmacokinetics of morphine in patients with severe renal impairment have not been conducted.

13 NONCLINICAL TOXICOLOGY

13.1 Carcinogenesis, Mutagenesis, Impairment of Fertility

Carcinogenesis

Long-term studies in animals to evaluate the carcinogenic potential of morphine have not been conducted.

Mutagenesis

No formal studies to assess the mutagenic potential of morphine have been conducted. In the published literature, morphine was found to be mutagenic in vitro increasing DNA fragmentation in human T-cells. Morphine was reported to be mutagenic in the in vivo mouse micronucleus assay and positive for the induction of chromosomal aberrations in mouse spermatids and murine lymphocytes. Mechanistic studies suggest that the in vivo clastogenic effects reported with morphine in mice may be related to increases in glucocorticoid levels produced by morphine in this species. In contrast to the above positive findings, in vitro studies in the literature have also shown that morphine did not induce chromosomal aberrations in human leukocytes or translocations or lethal mutations in Drosophila.

Impairment of Fertility

No formal nonclinical studies to assess the potential of morphine to impair fertility have been conducted.

Several nonclinical studies from the literature have demonstrated adverse effects on male fertility in the rat from exposure to morphine. One study in which male rats were administered morphine sulfate subcutaneously prior to mating (up to 30 mg/kg twice daily) and during mating (20 mg/kg twice daily) with untreated females, a number of adverse reproductive effects including reduction in total pregnancies and higher incidence of pseudopregnancies at 20 mg/kg/day (3.2 times the HDD) were reported.

Studies from the literature have also reported changes in hormonal levels in male rats (i.e. testosterone, luteinizing hormone) following treatment with morphine at 10 mg/kg/day or greater (1.6 times the HDD).

Female rats that were administered morphine sulfate intraperitoneally prior to mating exhibited prolonged estrous cycles at 10 mg/kg/day (1.6 times the HDD).

Exposure of adolescent male rats to morphine has been associated with delayed sexual maturation and following mating to untreated females, smaller litters, increased pup mortality, and/or changes in reproductive endocrine status in adult male offspring have been reported (estimated 5 times the plasma levels at the HDD).

16 HOW SUPPLIED/STORAGE AND HANDLING

Morphine Sulfate Tablets

15 mg tablet: white, biconvex tablets scored on one side and product identification "54 733" debossed on the other side.

NDC 0054-0235-24: 100 (4 x 25) Unit-Dose Tablets

NDC 0054-0235-25: Bottle of 100 Tablets

30 mg tablets: white, biconvex tablets scored on one side and product identification "54 262" debossed on the other side.

NDC 0054-0236-24: 100 (4 x 25) Unit-Dose Tablets

NDC 0054-0236-25: Bottle of 100 Tablets

Storage

Store at 20° to 25°C (68° to 77°F). [See USP Controlled Room Temperature.]

Protect from moisture.

17 PATIENT COUNSELING INFORMATION

Advise the patient to read the FDA-approved patient labeling (Medication Guide).

Addiction, Abuse, and Misuse

Inform patients that the use of Morphine Sulfate Tablets, even when taken as recommended, can result in addiction, abuse, and misuse, which can lead to overdose and death [see Warnings and Precautions (5.1)]. Instruct patients not to share Morphine Sulfate Tablets with others and to take steps to protect morphine sulfate from theft or misuse.

Life-Threatening Respiratory Depression

Inform patients of the risk of life-threatening respiratory depression, including information that the risk is greatest when starting Morphine Sulfate Tablets or when the dosage is increased, and that it can occur even at recommended dosages [see Warnings and Precautions (5.2)]. Advise patients how to recognize respiratory depression and to seek medical attention if breathing difficulties develop.

Accidental Ingestion

Inform patients that accidental ingestion, especially by children, may result in respiratory depression or death [see Warnings and Precautions (5.2)]. Instruct patients to take steps to store Morphine Sulfate Tablets securely and to dispose of unused Morphine Sulfate Tablets by flushing the unused tablets down the toilet.

Interactions with Benzodiazepines and Other CNS Depressants

Inform patients and caregivers that potentially fatal additive effects may occur if Morphine Sulfate Tablets are used with benzodiazepines or other CNS depressants, including alcohol, and not to use these concomitantly unless supervised by a healthcare provider [see Warnings and Precautions (5.4), Drug Interactions (7)].

Serotonin Syndrome

Inform patients that opioids could cause a rare but potentially life-threatening condition resulting from concomitant administration of serotonergic drugs. Warn patients of the symptoms of serotonin syndrome and to seek medical attention right away if symptoms develop. Instruct patients to inform their physicians if they are taking, or plan to take serotonergic medications [see Drug Interactions (7)].

MAOI Interaction

Inform patients not to take Morphine Sulfate Tablets while using any drugs that inhibit monoamine oxidase. Patients should not start MAOIs while taking Morphine Sulfate Tablets [see Warnings and Precautions (5.6), Drug Interactions (7)].

Adrenal Insufficiency

Inform patients that opioids could cause adrenal insufficiency, a potentially life-threatening condition. Adrenal insufficiency may present with non-specific symptoms and signs such as nausea, vomiting, anorexia, fatigue, weakness, dizziness, and low blood pressure. Advise patients to seek medical attention if they experience a constellation of these symptoms [see Warnings and Precautions (5.7)].

Important Administration Instructions

Instruct patients how to properly take Morphine Sulfate Tablets. Advise patients not to adjust the dose of morphine sulfate without consulting with a physician or other healthcare professional.

If patients have been receiving treatment with Morphine Sulfate Tablets for more than a few weeks and cessation of therapy is indicated, counsel them on the importance of safely tapering the dose as abrupt discontinuation of the medication could precipitate withdrawal symptoms. Provide a dose schedule to accomplish a gradual discontinuation of the medication [see Dosage and Administration (2.4)].

Hypotension

Inform patients that Morphine Sulfate Tablets may cause orthostatic hypotension and syncope. Instruct patients how to recognize symptoms of low blood pressure and how to reduce the risk of serious consequences should hypotension occur (e.g., sit or lie down, carefully rise from a sitting or lying position) [see Warnings and Precautions (5.8)].

Anaphylaxis

Inform patients that anaphylaxis have been reported with ingredients contained in Morphine Sulfate Tablets. Advise patients how to recognize such a reaction and when to seek medical attention [see Contraindications (4), Adverse Reactions (6)].

Pregnancy

Neonatal Opioid Withdrawal Syndrome: Inform patients of reproductive potential that prolonged use of Morphine Sulfate Tablets during pregnancy can result in neonatal opioid withdrawal syndrome, which may be life-threatening if not recognized and treated [see Warnings and Precautions (5.3), Use in Specific Populations (8.1)].

Embryo-Fetal Toxicity: Inform female patients of reproductive potential that Morphine Sulfate Tablets can cause fetal harm and to inform their healthcare provider of a known or suspected pregnancy [see Use in Specific Populations (8.1)].

Lactation

Advise nursing mothers to monitor infants for increased sleepiness (more than usual), breathing difficulties, or limpness. Instruct nursing mothers to seek immediate medical care if they notice these signs [see Use in Specific Populations (8.2)].

Infertility

Inform patients that chronic use of opioids may cause reduced fertility. It is not known whether these effects on fertility are reversible [see Adverse Reactions (6)].

Driving or Operating Heavy Machinery

Inform patients that Morphine Sulfate Tablets may impair the ability to perform potentially hazardous activities such as driving a car or operating heavy machinery. Advise patients not to perform such tasks until they know how they will react to the medication [see Warnings and Precautions (5.13)].

Constipation

Advise patients of the potential for severe constipation, including management instructions and when to seek medical attention [see Adverse Reactions (6)].

Disposal of Unused Morphine Sulfate Tablets

Advise patients to dispose of unused Morphine Sulfate Tablets by flushing down the toilet.

Distr. by: West-Ward
Pharmaceuticals Corp.
Eatontown, NJ 07724

10004596/07

Revised December 2016

MEDICATION GUIDE

Morphine Sulfate (mor-pheen) Tablets CII

Rx only

Morphine Sulfate Tablets are:

•
A strong prescription pain medicine that contains an opioid (narcotic) that is used to manage short term (acute) and long term (chronic) pain severe enough to require an opioid pain medicine, when other pain treatments such as non-opioid pain medicines do not treat your pain well enough or you cannot tolerate them.
•
An opioid pain medicine that can put you at risk for overdose and death. Even if you take your dose correctly as prescribed you are at risk for opioid addiction, abuse, and misuse that can lead to death.

Important information about Morphine Sulfate Tablets:

•
Get emergency help right away if you take too much Morphine Sulfate Tablets (overdose). When you first start taking Morphine Sulfate Tablets, when your dose is changed, or if you take too much (overdose), serious or life-threatening breathing problems that can lead to death may occur.
•
Taking Morphine Sulfate Tablets with other opioid medicines, benzodiazepines, alcohol, or other central nervous system depressants (including street drugs) can cause severe drowsiness, decreased awareness, breathing problems, coma, and death.
•
Never give anyone else your Morphine Sulfate Tablets. They could die from taking it. Store Morphine Sulfate Tablets away from children and in a safe place to prevent stealing or abuse. Selling or giving away Morphine Sulfate Tablets is against the law.

Do not take Morphine Sulfate Tablets if you have:

•
Severe asthma, trouble breathing, or other lung problems.
•
A bowel blockage or have narrowing of the stomach or intestines.
•
An allergy to morphine.

Before taking Morphine Sulfate Tablets, tell your healthcare provider if you have a history of:

•
Head injury, seizures.

•
Liver, kidney, thyroid problems.

•
Problems urinating.

•
Pancreas or gallbladder problems.

•
Abuse of street or prescription drugs, alcohol addiction, or mental health problems.

Tell your healthcare provider if you are:

•
Pregnant or planning to become pregnant. Prolonged use of morphine sulfate during pregnancy can cause withdrawal.
•
Breastfeeding. Morphine sulfate passes into breast milk and may harm your baby.
•
Taking prescription or over-the-counter medicines, vitamins, or herbal supplements. Taking Morphine Sulfate Tablets with certain other medicines can cause serious side effects that could lead to death.

When taking Morphine Sulfate Tablets:

•
Do not change your dose. Take Morphine Sulfate Tablets exactly as prescribed by your healthcare provider. Use the lowest dose possible for the shortest time needed.
•
Take your prescribed dose every 4 hours as needed for pain. Do not take more than your prescribed dose. If you miss a dose, take your next dose at your usual time.
•
Call your healthcare provider if the dose you are taking does not control your pain.
•
If you have been taking Morphine Sulfate Tablets regularly, do not stop taking morphine sulfate without talking to your healthcare provider.
•
After you stop taking Morphine Sulfate Tablets, flush unused Morphine Sulfate Tablets down the toilet.

While taking Morphine Sulfate Tablets DO NOT:

•
Drive or operate heavy machinery, until you know how morphine sulfate affects you. Morphine Sulfate Tablets can make you sleepy, dizzy, or lightheaded.
•
Drink alcohol or use prescription or over-the-counter medicines that contain alcohol. Using products containing alcohol during treatment with Morphine Sulfate Tablets may cause you to overdose and die.

The possible side effects of Morphine Sulfate Tablets:

•
Constipation, nausea, sleepiness, vomiting, tiredness, headache, dizziness, abdominal pain. Call your healthcare provider if you have any of these symptoms and they are severe.

Get emergency medical help if you have:

•
Trouble breathing, shortness of breath, fast heartbeat, chest pain, swelling of your face, tongue, or throat, extreme drowsiness, light-headedness when changing positions, feeling faint, agitation, high body temperature, trouble walking, stiff muscles, or mental changes such as confusion.

These are not all the possible side effects of Morphine Sulfate Tablets. Call your doctor for medical advice about side effects. You may report side effects to FDA at 1-800-FDA-1088. For more information go to dailymed.nlm.nih.gov.

Distr. by: West-Ward

Pharmaceuticals Corp.

Eatontown NJ 07724

For more information, please call 1-800-962-8364.

This Medication Guide has been approved by the U.S. Food and Drug Administration.

10004596/07

Revised December 2016